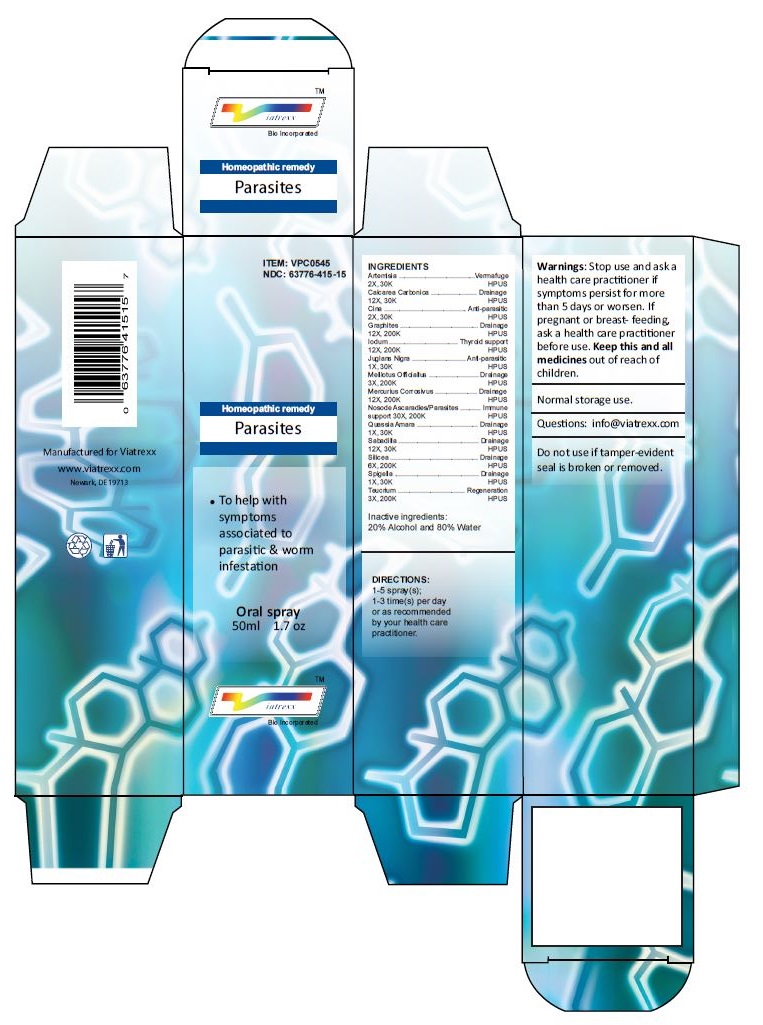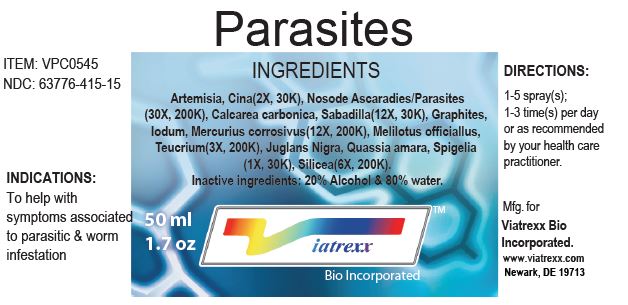 DRUG LABEL: Parasites
NDC: 63776-415 | Form: SPRAY
Manufacturer: VIATREXX BIO INCORPORATED
Category: homeopathic | Type: HUMAN OTC DRUG LABEL
Date: 20221130

ACTIVE INGREDIENTS: WORMWOOD 30 [kp_C]/1 mL; ARTEMISIA CINA PRE-FLOWERING TOP 30 [kp_C]/1 mL; AMOEBA PROTEUS 200 [kp_C]/1 mL; FLUKE, UNSPECIFIED 200 [kp_C]/1 mL; OYSTER SHELL CALCIUM CARBONATE, CRUDE 30 [kp_C]/1 mL; SCHOENOCAULON OFFICINALE SEED 30 [kp_C]/1 mL; GRAPHITE 200 [kp_C]/1 mL; IODINE 200 [kp_C]/1 mL; MERCURIC CHLORIDE 200 [kp_C]/1 mL; MELILOTUS OFFICINALIS TOP 200 [kp_C]/1 mL; TEUCRIUM MARUM 200 [kp_C]/1 mL; JUGLANS NIGRA WHOLE 30 [kp_C]/1 mL; QUASSIA AMARA WOOD 30 [kp_C]/1 mL; SPIGELIA MARILANDICA ROOT 30 [kp_C]/1 mL; SILICON DIOXIDE 200 [kp_C]/1 mL
INACTIVE INGREDIENTS: ALCOHOL; WATER

Parasites

Active Ingredients

Artemisia (2X, 30K), Cina (2X, 30K), Nosode Ascaradies/Parasites (30X, 200K), Calcarea Carbonica (12X, 30K), Sabadilla (12X, 30K), Graphites (12X, 200K), Iodum (12X, 200K), Mercurius Corrosivus (12X, 200K), Melilotus Officiallus (3X, 200K), Teucrium (3X, 200K), Juglans Nigra, Quassia Amara (1X, 30K), Spigelia (1X, 30K), Silicea (6X, 200K).

Purpose:

Artemisia | Vermafuge
Calcarea Carbonica | Drainage
Cina | Anti-parasitic
Graphites | Drainage
Iodum | Thyroid support
Juglans Nigra | Anti-parasitic
Melilotus Officiallus | Drainage
Mercurius Corrosivus | Drainage
Nosode Ascaradies/Parasites | Immune support
Quassia Amara | Drainage
Sabadilla | Drainage
Silicea | Drainage
Spigelia | Drainage
Teucrium | Regeneration

Uses

To help with symptoms associated to parasitic & worm infestation

Warnings

Stop use and ask a health care practitioner if symptoms persist for more than five days or worsen. If pregnant or breastfeeding, ask a health care practitioner before use.

Dosage

1-5 spray(s); 1-3 time(s) per day or as recommended by your health care practitioner.

KEEP OUT OF REACH OF CHILDREN

Keep this and all medicines out of reach of children.

Other Ingredients

20% Alcohol and 80% Water.

Other Information

Normal storage use.
Do not use if tamper-evident seal is broken or removed.

Questions

info@viatrexx.com

Principal Display Panel

ITEM: VPC0545
NDC 63776-415-15
Homeopathic remedy
Parasites
• To help with symptoms associated to parasitic & worm infestation
Oral spray
50ml 1.7 oz
Viatrexx™ Bio Incorporated
Manufactured by Viatrexx
www.viatrexx.com
Newark, DE 19713

Parasites
50 ml
1.7 oz
Viatrexx™ Bio Incorporated
ITEM: VPC0545
NDC: 63776-415-145
INDICATIONS:
To help with symptoms associated to parasitic & worm infestation
DIRECTIONS:
1-5 spray(s); 1-3 time(s) per day or as recommended by your health care practitioner.
Mfg. for
Viatrexx Bio Incorporated.
www.viatrexx.com
Newark, DE 19713